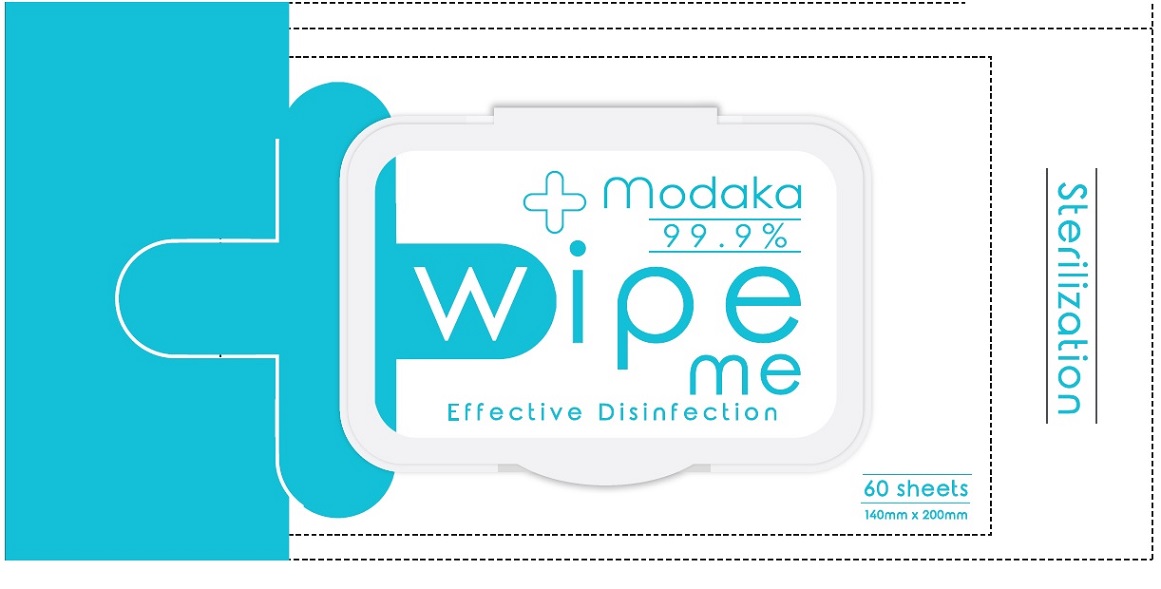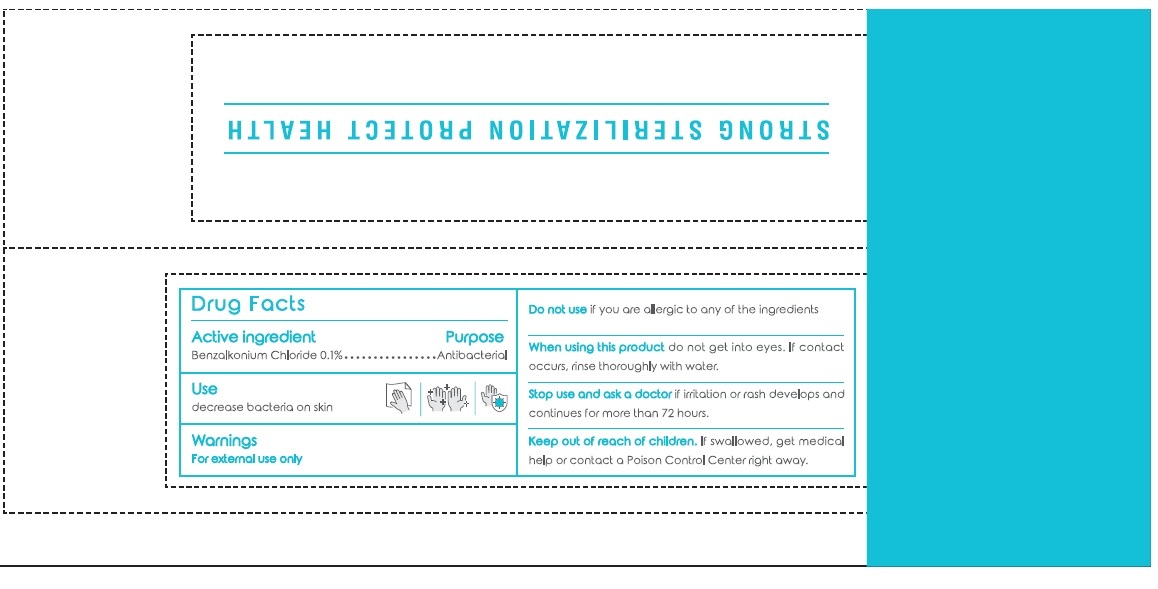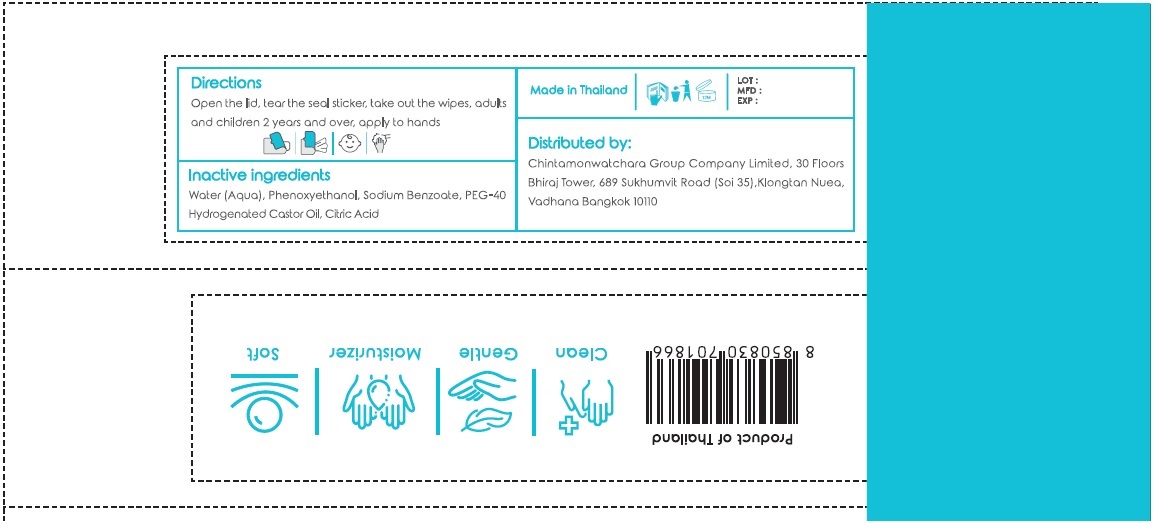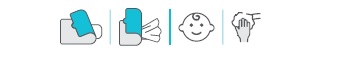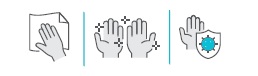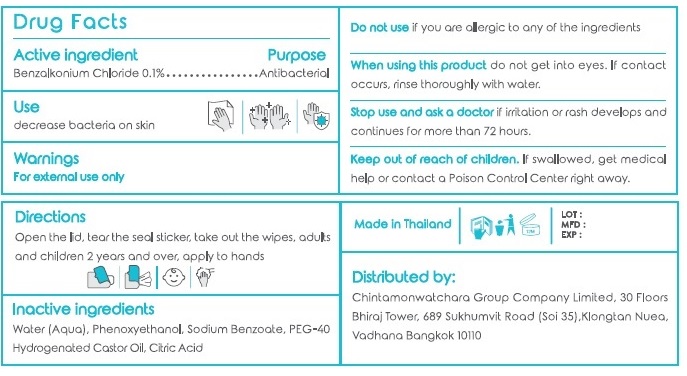 DRUG LABEL: Modaka Wipe Me
NDC: 77586-002 | Form: CLOTH
Manufacturer: DERMA INNOVATION COMPANY LIMITED
Category: otc | Type: HUMAN OTC DRUG LABEL
Date: 20200916

ACTIVE INGREDIENTS: BENZALKONIUM CHLORIDE 0.1 g/100 mL
INACTIVE INGREDIENTS: WATER; PHENOXYETHANOL; SODIUM BENZOATE; POLYOXYL 40 HYDROGENATED CASTOR OIL; CITRIC ACID MONOHYDRATE

Modaka Wipe Me

Active ingredient

Benzalkonium Chloride 0.1%

Purpose

Antibacterial

Use

decrease bacteria on skin

Warnings

For external use only

Do not use if you are allergic to any of the ingredients

When using this product do not get into eyes. If contact occurs, rinse thoroughly with water.

Stop use and ask a doctor if irritation or rash develops and continues for more than 72 hours.

Keep out of reach of children. If swallowed, get medical help or contact a Poison Control Center right away.

Directions

Open the lid, tear the seal sticker, take out the wipes, adults and children 2 years and over, apply to hands

Inactive ingredients

Water (Aqua), Phenoxyethanol, Sodium Benzoate, PEG-40 Hydrogenated Castor Oil, Citric Acid

99.9%

Effective Disinfection

Sterilization

STRONG STERILIZATION PROTECT HEALTH

Clean

Gentle

Moisturizer

Soft

Made in Thailand

Distributed by:

Chintamonwatchara Group Company Limited, 30 Floors

Bhiraj Tower, 689 Sukhumvit Road (Soi 35), Klongtan Nuea, Vadhana Bangkok 10110